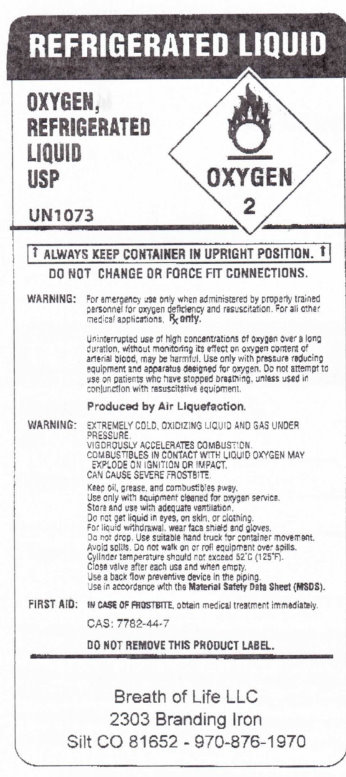 DRUG LABEL: Oxygen, Refrigerated
NDC: 52472-100 | Form: GAS
Manufacturer: Breath of Life LLC
Category: prescription | Type: HUMAN PRESCRIPTION DRUG LABEL
Date: 20100712

ACTIVE INGREDIENTS: OXYGEN 1 L/1 L

Refrigerated Liquid Oxygen, Refrigerated Liquid USP

PACKAGE LABEL

Refrigerated Liquid
Oxygen, Refrigerated Liquid USP
UN1073
Always keep container in upright position.
Do not change or force fit connections.
Warning: For emergency use only when administered by properly trained personnel for oxygen deficiency and resuscitation. For all other medical applications. Rx only.
Uninterrupted use of high concentrations of oxygen over a long duration, without monitoring its effect on oxygen content of arterial blood, may be harmful. Use only with pressure reducing
equipment and apparatus designed for oxygen. Do not attempt to use on patients who have stopped breathing, unless used in conjunction with resuscitative equipment.
Produced by Air Liquefaction.
Warning: Extremely cold, oxidizing liquid and gas under pressure.
Vigorously accelerates combustion.
Combustibles in contact with liquid oxygen may explode on ignition or impact.
Can cause severe frostbite.
Keep oil, grease and combustible away.
Use only with equipment cleaned for oxygen service.
Store and use with adequate ventilation.
Do not get liquid in eyes , on skin, or clothing.
For liquid withdrawal, wear face shield and gloves.
Do not drop.
Use suitable hand truck for container movement.
Avoid spills. Do not walk on or roll equipment over spills.
Cylinder temperature should not exceed 52 degrees C (125 degrees F)
Close valve after each use and when empty.
Use a back flow preventive device in the piping.
Use in accordance with Material Safety Data Sheet (MSDS).
First Aid: In case of frostbite, obtain medical treatment immediately.
CAS: 7782-44-7
Do not remove this product label.
Breath of Life LLC
2303 Branding Iron
Silt CO 81652
970-876-1970